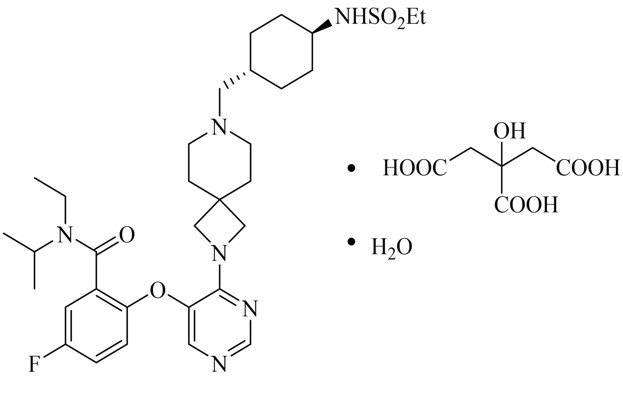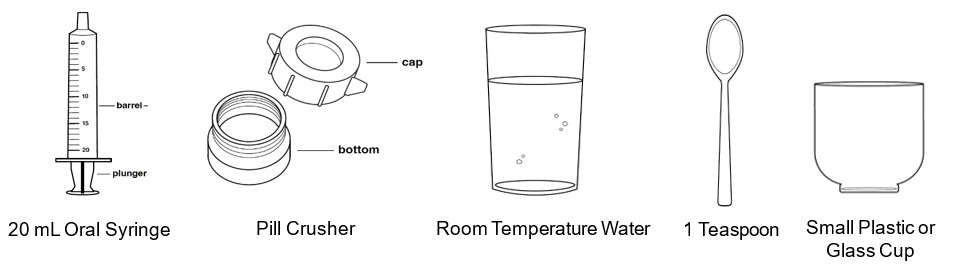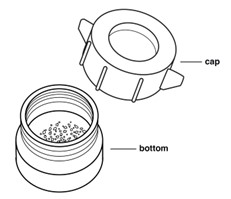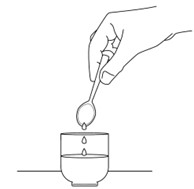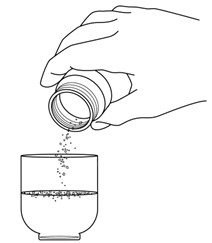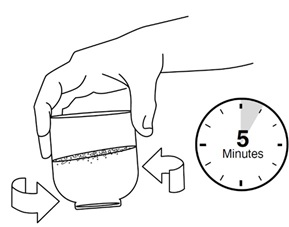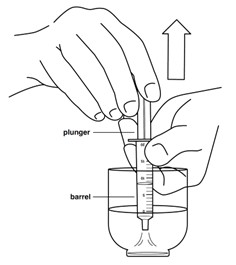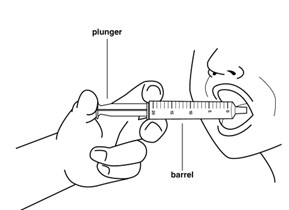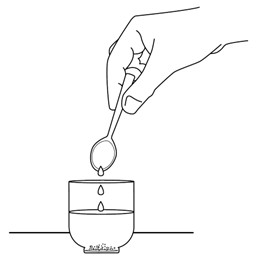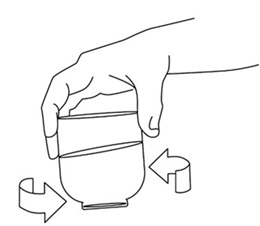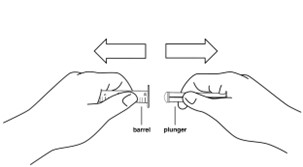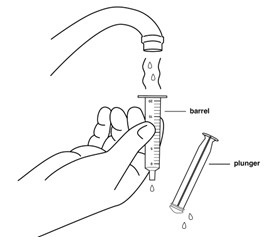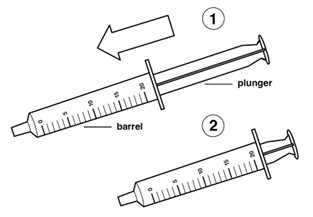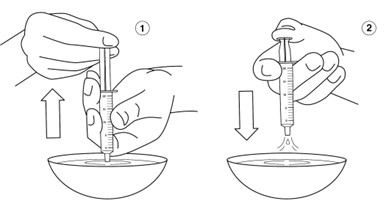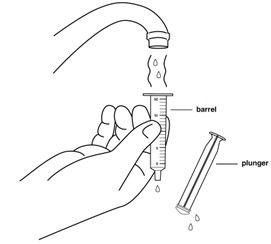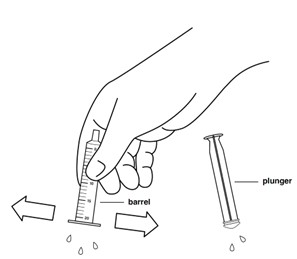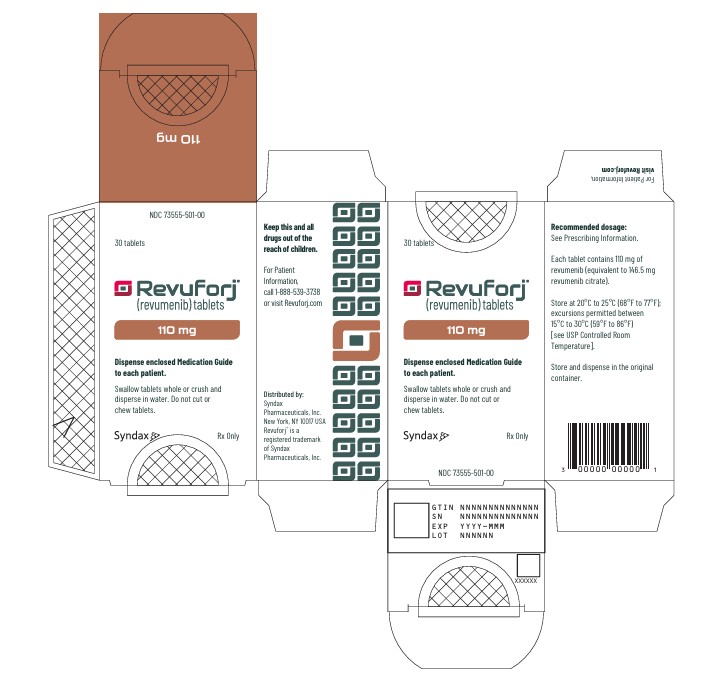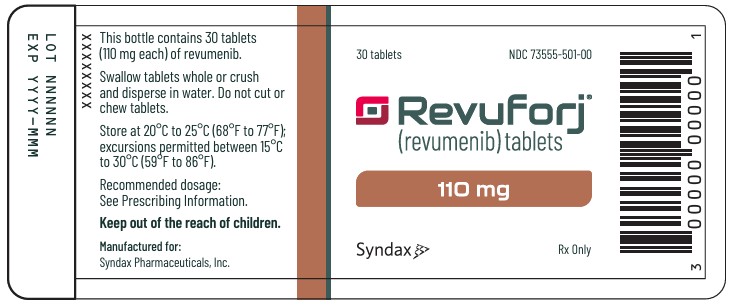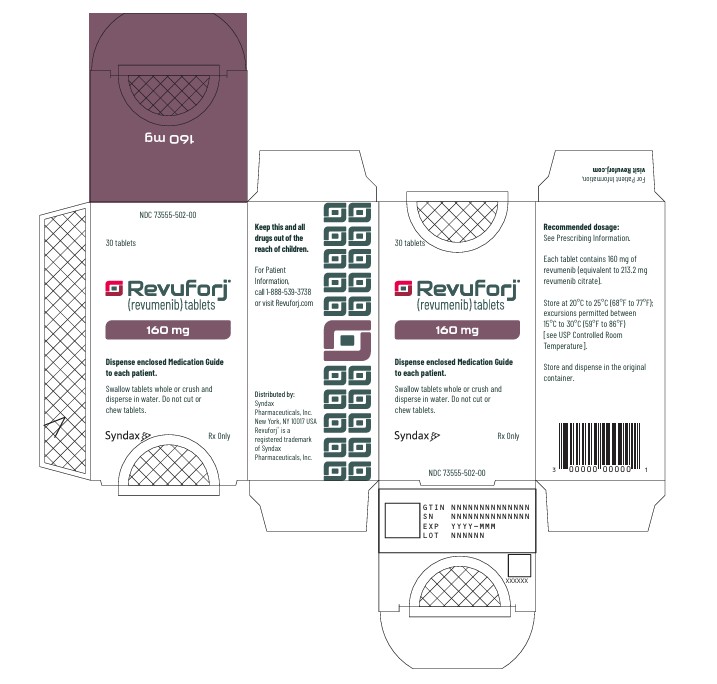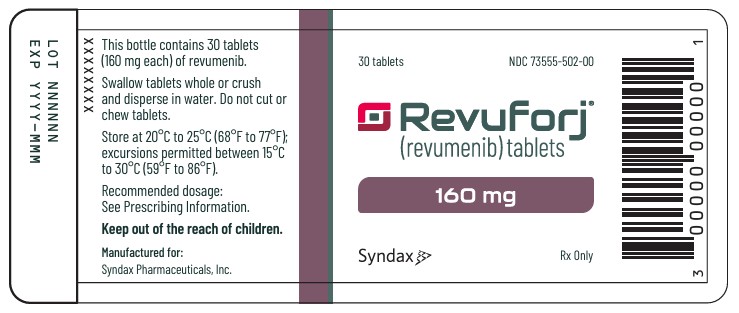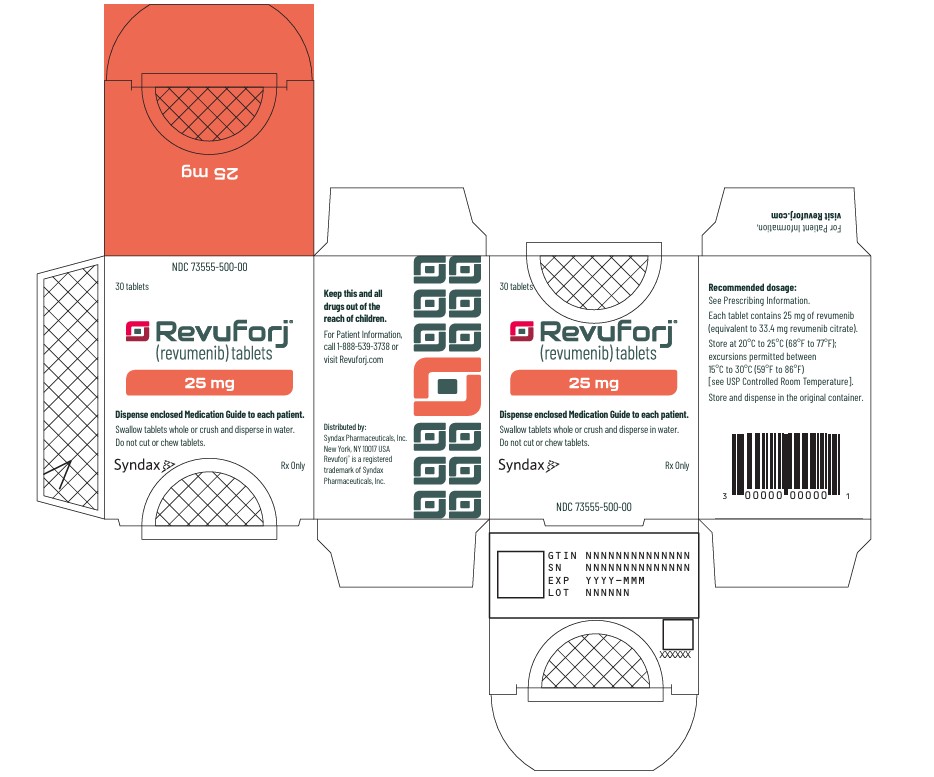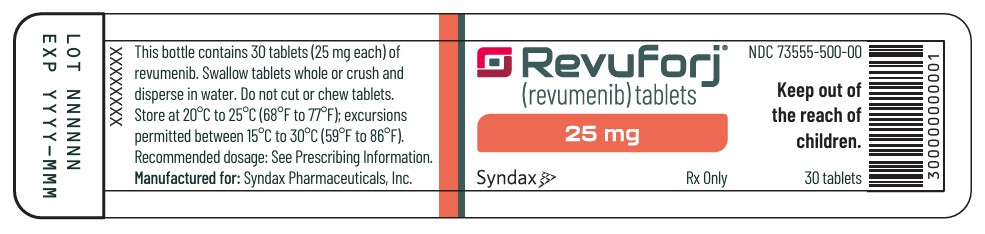 DRUG LABEL: Revuforj
NDC: 73555-500 | Form: TABLET, FILM COATED
Manufacturer: Syndax Pharmaceuticals, Inc.
Category: prescription | Type: HUMAN PRESCRIPTION DRUG LABEL
Date: 20260204

ACTIVE INGREDIENTS: revumenib citrate 25 mg/1 1

HIGHLIGHTS OF PRESCRIBING INFORMATION

These highlights do not include all the information needed to use REVUFORJ safely and effectively. See full prescribing information for REVUFORJ.
REVUFORJ (revumenib) tablets for oral use
Initial U.S. Approval: 2024

WARNING: DIFFERENTIATION SYNDROME, QTc PROLONGATION and TORSADES DE POINTES

WARNING: DIFFERENTIATION SYNDROME, and QTc PROLONGATION and TORSADES DE POINTES

See full prescribing information for complete boxed warning.

Differentiation syndrome, which can be fatal, has occurred with REVUFORJ. If differentiation syndrome is suspected, immediately initiate corticosteroid therapy and hemodynamic monitoring until symptom resolution (2.3, 5.1)

QTc prolongation and Torsades de Pointes have occurred in patients receiving REVUFORJ. Correct hypokalemia and hypomagnesemia prior to and during treatment. Do not initiate REVUFORJ in patients with QTcF > 450 msec. If QTc interval prolongation occurs, interrupt, reduce, or permanently discontinue REVUFORJ. (2.3, 5.2).

1 INDICATIONS AND USAGE

REVUFORJ is a menin inhibitor indicated for:

- the treatment of relapsed or refractory acute leukemia with a lysine methyltransferase 2A gene (KMT2A) translocation as determined by an FDA-authorized test in adult and pediatric patients 1 year and older. (1)
- the treatment of relapsed or refractory acute myeloid leukemia (AML) with a susceptible nucleophosmin 1 (NPM1) mutation in adult and pediatric patients 1 year and older who have no satisfactory alternative treatment options. (1)

2 DOSAGE AND ADMINISTRATION

- Select patients for treatment with REVUFORJ based on the presence of a KMT2A translocation or an NPM1 mutation. (2.1)
- Administer REVUFORJ orally twice daily fasted or with a low-fat meal at approximately the same time each day. (2.2)
- See Full Prescribing Information for recommended REVUFORJ dosage regimen, dosage modifications, and administration instructions. (2.2, 2.3)

3 DOSAGE FORMS AND STRENGTHS

Tablets: 25 mg, 110 mg, 160 mg (3)

4 CONTRAINDICATIONS

None. (4)

5 WARNINGS AND PRECAUTIONS

Embryo-Fetal Toxicity: Can cause fetal harm. Advise females of reproductive potential and males with female partners of reproductive potential of potential risk to a fetus and to use effective contraception. (5.3, 8.1, 8.3)

6 ADVERSE REACTIONS

The most common adverse reactions (≥ 20%) including laboratory abnormalities, are phosphate increased, hemorrhage, nausea, infection without identified pathogen, aspartate aminotransferase increased, alanine aminotransferase increased, creatinine increased, musculoskeletal pain, febrile neutropenia, electrocardiogram QT prolonged, potassium decreased, parathyroid hormone intact increased, alkaline phosphatase increased, diarrhea, bacterial infection, triglycerides increased, differentiation syndrome, fatigue, edema, viral infection, phosphate decreased, decreased appetite, and constipation. (6.1)

To report SUSPECTED ADVERSE REACTIONS, contact Syndax Pharmaceuticals, Inc., at 1-888-539-3REV or FDA at 1-800-FDA-1088 or www.fda.gov/medwatch.

7 DRUG INTERACTIONS

- Strong CYP3A4 Inhibitors: Reduce the REVUFORJ dose. (2.2, 7.1)
- Strong or moderate CYP3A4 Inducers: Avoid concomitant use with REVUFORJ. (7.1)
- QTc Prolonging Drugs: Avoid concomitant use with REVUFORJ. If concomitant use is unavoidable, monitor patients more frequently for QTc interval prolongation. (5.2, 7.1)

8 USE IN SPECIFIC POPULATIONS

Lactation: Advise not to breastfeed (8.2)

FULL PRESCRIBING INFORMATION

WARNING: DIFFERENTIATION SYNDROME, QTc PROLONGATION and TORSADES DE POINTES

Differentiation syndrome, which can be fatal, has occurred with REVUFORJ. Signs and symptoms may include fever, dyspnea, hypoxia, pulmonary infiltrates, pleural or pericardial effusions, rapid weight gain or peripheral edema, hypotension, and renal dysfunction. If differentiation syndrome is suspected, immediately initiate corticosteroid therapy and hemodynamic monitoring until symptom resolution. [see Dosage and Administration (2.3), Warnings and Precautions (5.1), and Adverse Reactions (6.1)].

QTc prolongation and Torsades de Pointes have occurred in patients receiving REVUFORJ. Correct hypokalemia and hypomagnesemia prior to and during treatment. Do not initiate REVUFORJ in patients with QTcF > 450 msec. If QTc interval prolongation occurs, interrupt, reduce, or permanently discontinue REVUFORJ. [see Dosage and Administration (2.3), Warnings and Precautions (5.2), and Adverse Reactions (6.1)]

1 INDICATIONS AND USAGE

Relapsed or Refractory Acute Leukemia

- REVUFORJ is indicated for the treatment of relapsed or refractory acute leukemia with a lysine methyltransferase 2A gene (KMT2A) translocation as determined by an FDA-authorized test in adult and pediatric patients 1 year and older.
- REVUFORJ is indicated for the treatment of relapsed or refractory acute myeloid leukemia with a susceptible nucleophosmin 1 (NPM1) mutation [see Dosage and Administration (2.1), Clinical Pharmacology (12.1), and Clinical Studies (14.1)] in adult and pediatric patients 1 year and older who have no satisfactory alternative treatment options.

2 DOSAGE AND ADMINISTRATION

2.1 Patient Selection

Relapsed or Refractory Acute Leukemia with a KMT2A Translocation

Select patients for treatment with REVUFORJ based on the presence of a KMT2A translocation [see Clinical Studies (14.1)]. Information on FDA authorized tests for the detection of a KMT2A translocation to determine eligibility for treatment is available at https://www.accessdata.fda.gov/scripts/cdrh/cfdocs/cfpmn/denovo.cfm?id=DEN240067

Relapsed or Refractory Acute Myeloid Leukemia with an NPM1 mutation

Select patients for treatment with REVUFORJ based on the presence of an NPM1 mutation [see Clinical Pharmacology (12.1) and Clinical Studies (14.2)]. An FDA-approved companion diagnostic for the detection of an NPM1 mutation is not currently available.

2.2 Recommended Dosage

The recommended dosage of REVUFORJ varies by patient weight and concomitant use of strong CYP3A4 inhibitors. See Table 1 for the recommended dosage for patients 1 year and older. Do not start REVUFORJ until the WBC is reduced to less than 25 Gi/L. Continue REVUFORJ until disease progression or unacceptable toxicity. For patients without disease progression or unacceptable toxicity, treat for a minimum of 6 months to allow time for clinical response.

Table 1. REVUFORJ Recommended Dosage for Patients 1 Year and Older
Patient Weight | Without Strong CYP3A4 Inhibitors | With Strong CYP3A4 Inhibitors
40 kg or more | 270 mg orally twice daily | 160 mg orally twice daily
Less than 40 kg | 160 mg/m^2 orally twice daily* | 95 mg/m^2 orally twice daily*
*See Table 2 for the total tablet dosage by BSA (body surface area) for patients weighing less than 40 kg.

Table 2: Recommended Dosage using Tablets* for Patients Weighing Less than 40 kg
BSA (m^2) | REVUFORJ Dosage for 160 mg/m^2 | REVUFORJ Dosage for 95 mg/m^2
1.4 | 220 mg twice daily | 135 mg twice daily
1.3 | 220 mg twice daily | 135 mg twice daily
1.2 | 185 mg twice daily | 110 mg twice daily
1.1 | 185 mg twice daily | 110 mg twice daily
1 | 160 mg twice daily | 100 mg twice daily
0.9 | 135 mg twice daily | 75 mg twice daily
0.8 | 135 mg twice daily | 75 mg twice daily
0.7 | 110 mg twice daily | 50 mg twice daily
0.6 | 100 mg twice daily | 50 mg twice daily
0.5 | 75 mg twice daily | 50 mg twice daily
0.4 | 50 mg twice daily | 25 mg twice daily
* If needed, attain the desired dose by combining different strengths of REVUFORJ tablets.

- If the strong CYP3A4 inhibitor is discontinued, increase the REVUFORJ dose after at least 5 half-lives of the strong CYP3A4 inhibitor to the recommended dosage without strong CYP3A4 inhibitors (Table 1).
- Concurrent use of standard intrathecal chemotherapy prophylaxis is recommended for patients with risk of central nervous system relapse.

Administration:

- Correct hypokalemia, hypomagnesemia, and other electrolyte abnormalities prior to treatment.
- Administer REVUFORJ twice daily fasted or with a low-fat meal (e.g., meals with approximately 400 calories, 25% or less fat).
- Administer REVUFORJ orally around the same time each day.
- Advise patients to swallow tablets whole and to not cut or chew tablets. If patients are unable to swallow tablets, they may be crushed and dispersed in water and taken within 2 hours of preparation [see Instructions for Use].
- If a dose of REVUFORJ is missed or not taken at the usual time, administer the dose as soon as possible on the same day and at least 12 hours prior to the next scheduled dose. Return to the normal schedule the following day. Do not administer 2 doses within 12 hours.

2.3 Dosage Modifications for Adverse Reactions

Assess blood counts, electrolytes, and liver enzymes prior to the initiation of REVUFORJ and monthly thereafter. Perform an electrocardiogram (ECG) prior to the initiation of REVUFORJ, at least once a week for the first 4 weeks, and at least monthly thereafter. Monitor for QTc interval prolongation and manage any abnormalities promptly [see Warnings and Precautions (5.2) and Adverse Reactions (6.1)].

Interrupt dosing or reduce dose for adverse reactions as per Table 3. Dose levels for dose reductions are listed in Table 4, Table 5, and Table 6.

Table 3. Recommended Management and Dosage Modifications for Adverse Reactions
Adverse reaction | Recommended action
Differentiation Syndrome [see Warnings and Precautions (5.1)] | - If differentiation syndrome is suspected, administer systemic corticosteroids and initiate hemodynamic monitoring until symptom resolution and for a minimum of 3 days. [see Warnings and Precautions (5.1)]. - Interrupt REVUFORJ if severe signs and/or symptoms persist for more than 48 hours after initiation of systemic corticosteroids, or earlier for life-threatening symptoms such as pulmonary symptoms requiring ventilator support [see Warnings and Precautions (5.1)]. Resume REVUFORJ at the same dose when signs and symptoms improve to Grade 1* or lower.
Noninfectious leukocytosis | - Initiate treatment with hydroxyurea in patients with an elevated or rapidly rising leukocyte count. Add leukapheresis if clinically indicated. - Taper hydroxyurea only after leukocytosis improves or resolves.
QTc interval greater than 480 msec to 500 msec [see Warnings and Precautions(5.2)] | - Interrupt REVUFORJ. - Check electrolyte levels. Correct hypokalemia and hypomagnesemia [see Warnings and Precautions (5.2)]. - Restart REVUFORJ at the same dose level after the QTc interval returns to less than or equal to 480 msec.
QTc interval greater than 500 msec (Grade 3*) [see Warnings and Precautions (5.2)] | - Interrupt REVUFORJ. - Check electrolyte levels. Correct hypokalemia and hypomagnesemia [see Warnings and Precautions (5.2)]. - Restart REVUFORJ at the reduced dose level** after the QTc interval returns to less than or equal to 480 msec.
QTc interval prolongation with signs/symptoms of life-threatening arrhythmia, Torsades de pointes, polymorphic ventricular tachycardia, signs/ symptoms of life-threatening arrhythmia (Grade 4*) [see Warnings and Precautions (5.2)]. | - Permanently discontinue REVUFORJ.
Potassium 3.6-3.9 mEq/L, and/or Magnesium 1.7-1.9 mg/dL or 0.66-0.81 mmol/L | - Supplement potassium and/or magnesium. - Continue REVUFORJ.
Potassium ≤ 3.5 mEq/L, and/or; Magnesium ≤ 1.6 mg/dL or; ≤ 0.65 mmol/L | - Supplement potassium and/or magnesium, and recheck levels within 24 hours. - On recheck of potassium and magnesium labs within 24 hours, if potassium is greater than 3.5 mEq/L and/or magnesium is greater than 1.6 mg/dL, continue REVUFORJ. If potassium is less than 3.5 mEq/L and/or magnesium is less than 1.6 mg/dL, hold REVUFORJ and continue supplementation; resume REVUFORJ at the same dose level when the correction is complete.
Other nonhematological adverse reactions Grade ≥ 3* [see Adverse Reactions (6.1)] | - Interrupt REVUFORJ until recovery to Grade 1* or baseline. - If recovered in ≤ 7 days, restart REVUFORJ at the same dose level. If the same Grade ≥ 3* toxicity recurs, interrupt REVUFORJ until recovery to Grade 1* or baseline. Restart REVUFORJ at the reduced dose level.** - If recovered in > 7 days, restart REVUFORJ at the reduced dose level.** If the same Grade ≥ 3* toxicity recurs, discontinue REVUFORJ.
Grade 4* neutropenia or thrombocytopenia [see Adverse Reactions (6.1)] | - Interrupt REVUFORJ until recovery to Grade ≤ 2* or baseline. - Restart REVUFORJ at the same dose level. - If Grade 4* neutropenia or thrombocytopenia recurs without attributable cause, interrupt REVUFORJ until recovery to Grade ≤ 3*. Restart REVUFORJ at the reduced dose level.**
Grade 3* or higher allergic reactions [see Adverse Reactions (6.1)] | - Permanently discontinue REVUFORJ.
*Grade 1 is mild, Grade 2 is moderate, Grade 3 is severe, Grade 4 is life-threatening. Severity as defined by National Cancer Institute Common Terminology Criteria for Adverse Events (NCI CTCAE version 5.0).
**See Tables 4, 5 and 6 for the reduced dose levels.

Table 4. REVUFORJ Dosage Reduction for Adverse Reactions in Patients NOT on Strong CYP3A4 Inhibitors
 | Patients Weighing 40 kg or Greater at Starting Dose 270 mg orally twice daily | Patients Weighing Less Than 40 kg at Starting Dose 160 mg/m^2 orally twice daily
Reduced Dose | 160 mg orally twice daily | 95 mg/m^2 orally twice daily*
**See Table 6 for BSA-based dosage recommendations for the reduced dosage of 95 mg/m^2 twice daily.

Table 5. REVUFORJ Dosage Reduction for Adverse Reactions in Patients on Strong CYP3A4 Inhibitors
 | Patients Weighing 40 kg or Greater at Starting Dose 160 mg orally twice daily | Patients Weighing Less Than 40 kg at Starting Dose 95 mg/m^2 orally twice daily
Reduced Dose | 110 mg orally twice daily | 65 mg/m^2 orally twice daily*
*See Table 6 for BSA-based dosage recommendations for the reduced dosage of 65 mg/m^2 twice daily.

Table 6: Recommended Reduced Dosage Using Tablets* for Patients Weighing Less than 40 kg
BSA (m^2) | REVUFORJ Dosage for 95 mg/m^2 | REVUFORJ Dosage for 65 mg/m^2
1.4 | 135 mg twice daily | 100 mg twice daily
1.3 | 135 mg twice daily | 75 mg twice daily
1.2 | 110 mg twice daily | 75 mg twice daily
1.1 | 110 mg twice daily | 75 mg twice daily
1 | 100 mg twice daily | 50 mg twice daily
0.9 | 75 mg twice daily | 50 mg twice daily
0.8 | 75 mg twice daily | 50 mg twice daily
0.7 | 50 mg twice daily | 50 mg twice daily
0.6 | 50 mg twice daily | 25 mg twice daily
0.5 | 50 mg twice daily | 25 mg twice daily
0.4 | 25 mg twice daily | 25 mg twice daily
* If needed, attain the desired dose by combining different strengths of REVUFORJ tablets.

3 DOSAGE FORMS AND STRENGTHS

Tablets:

- 25 mg of revumenib: Pink modified oval film-coated tablet debossed with “S” on one side and “25” on the other side.
- 110 mg of revumenib: Beige modified oval film-coated tablet debossed with “S” on one side and “110” on the other side.
- 160 mg of revumenib: Purple modified oval film-coated tablet debossed with “S” on one side and “160” on the other side.

4 CONTRAINDICATIONS

None.

5 WARNINGS AND PRECAUTIONS

5.1 Differentiation Syndrome

REVUFORJ can cause fatal or life-threatening differentiation syndrome (DS). Symptoms of differentiation syndrome, including those seen in patients treated with REVUFORJ, include fever, dyspnea, hypoxia, peripheral edema, pleuropericardial effusion, acute renal failure, rash, and/or hypotension.

In clinical trials, DS occurred in 60 (25%) of 241 patients treated with REVUFORJ at the recommended dosage for relapsed or refractory acute leukemia [see Adverse Reactions (6.1)]. Among those with a KMT2A translocation, DS occurred in 33% of patients with acute myeloid leukemia (AML), 33% of patients with mixed-phenotype acute leukemia (MPAL), and 9% of patients with acute lymphoblastic leukemia (ALL); DS occurred in 18% of patients with NPM1 mutated AML. DS was Grade 3 or 4 in 12% of patients and fatal in two patients. The median time to initial onset was 9 days (range 3-41 days). Some patients experienced more than 1 DS event. Treatment interruption was required for 7% of patients, and treatment was withdrawn for 1%.

Reduce the white blood cell count (WBC) to less than 25 Gi/L prior to starting REVUFORJ. If DS is suspected, immediately initiate treatment with systemic corticosteroids (e.g., dexamethasone 10 mg intravenously every 12 hours in adults or dexamethasone 0.25 mg/kg/dose intravenously every

12 hours in pediatric patients weighing less than 40 kg) for a minimum of 3 days and until resolution of signs and symptoms. Institute supportive measures and hemodynamic monitoring until improvement. Interrupt REVUFORJ if severe signs and/or symptoms persist for more than 48 hours after initiation of systemic corticosteroids, or earlier if life-threatening symptoms occur such as pulmonary symptoms requiring ventilator support. Restart steroids promptly if DS recurs after tapering corticosteroids [see Dosage and Administration (2.3)].

5.2 QTc Interval Prolongation and Torsades de Pointes

REVUFORJ can cause QT (QTc) interval prolongation and Torsades de Pointes [see Clinical Pharmacology (12.2)].

Of the 241 patients treated with REVUFORJ at the recommended dosage for relapsed or refractory acute leukemia in clinical trials, QTc interval prolongation was reported as an adverse reaction in 86 (36%) of patients. QTc interval prolongation was Grade 3 in 15% and Grade 4 in 2%. The heart-rate corrected QT interval (using Fridericia’s method) (QTcF) was greater than 500 msec in 10%, and the increase from baseline QTcF was greater than 60 msec in 24%. REVUFORJ dose reduction was required for 7% due to QTc interval prolongation [see Adverse Reactions (6.1)]. QTc prolongation occurred in 21% of the 34 patients less than 17 years old, 35% of the 146 patients 17 years to less than 65 years old, and in 46% of the 61 patients 65 years or older. One patient had a fatal outcome of cardiac arrest, and one patient had nonsustained Torsades de Pointes.

Correct electrolyte abnormalities, including hypokalemia and hypomagnesemia, prior to and throughout treatment with REVUFORJ. Perform an ECG prior to initiation of treatment with

REVUFORJ, and do not initiate REVUFORJ in patients with QTcF > 450 msec. Perform an ECG at least once a week for the first 4 weeks on treatment, and at least monthly thereafter [see Dosage and Administration (2.3)]. In patients with congenital long QTc syndrome, congestive heart failure, electrolyte abnormalities, or those who are taking medications known to prolong the QTc interval, more frequent ECG monitoring may be necessary. Concomitant use of REVUFORJ with drugs known to prolong the QTc interval may increase the risk of QTc interval prolongation. [see Drug Interactions (7.1), Clinical Pharmacology (12.2)].

Interrupt REVUFORJ if QTcF increases to greater than 480 msec and less than 500 msec, and restart REVUFORJ at the same dose twice daily after the QTcF interval returns to less than or equal to 480 msec. Interrupt REVUFORJ if QTcF increases to greater than 500 msec or by > 60 msec from baseline, and restart REVUFORJ twice daily at the lower dose level after the QTcF interval returns to less than or equal to 480 msec. Permanently discontinue REVUFORJ in patients with ventricular arrhythmias and in those who develop QTc interval prolongation with signs or symptoms of life- threatening arrhythmia [see Dosage and Administration (2.3)].

5.3 Embryo-Fetal Toxicity

Based on findings in animals and its mechanism of action, REVUFORJ can cause fetal harm when administered to a pregnant woman. In an animal reproduction study, oral administration of revumenib to pregnant rats during the period of organogenesis caused adverse developmental outcomes, including embryo-fetal mortality, malformations, and altered fetal growth at maternal exposures approximately 0.5 times the human exposure (AUC) at the recommended dose.

Advise pregnant women of the potential risk to a fetus. Advise females of reproductive potential and males with female partners of reproductive potential to use effective contraception during treatment with REVUFORJ and for 4 months after the last dose [see Use in Specific Populations (8.1, 8.3) and Clinical Pharmacology (12.3)].

6 ADVERSE REACTIONS

The following clinically significant adverse reactions are described elsewhere in the labeling:

- Differentiation Syndrome [see Warnings and Precautions (5.1)]
- QTc Interval Prolongation and Torsades de Pointes [see Warnings and Precautions (5.2)]

6.1 Clinical Trials Experience

Because clinical trials are conducted under widely varying conditions, adverse reaction rates observed in the clinical trials of a drug cannot be directly compared to rates in the clinical trials of another drug and may not reflect the rates observed in practice.

The safety of REVUFORJ reflects exposure in 241 patients (207 adult and 34 pediatric patients) with relapsed or refractory (R/R) acute leukemia with a KMT2A translocation or an NPM1 mutation treated with REVUFORJ at a dose approximately equivalent to 160 mg in adults orally twice daily with a strong CYP3A4 inhibitor [see Clinical Studies (14)]. The median duration of exposure to REVUFORJ was 2.5 months (range < 1 to 40 months), and 10% of patients were exposed for more than 6 months.

Fatal adverse reactions occurred in 9 (4%) patients who received REVUFORJ, including 4 with sudden death, 2 with differentiation syndrome, 2 with hemorrhage, and 1 with cardiac arrest. Serious adverse reactions were reported in 184 (76%) patients. The most frequent serious adverse reactions (≥ 10%) were infection (29%), febrile neutropenia (20%), bacterial infection (15%), differentiation syndrome (13%), and hemorrhage (11%).

Adverse reactions leading to dose interruption occurred in 49% of patients. The most common adverse reactions (≥ 5%) leading to dose interruption were electrocardiogram QT prolonged, infection, febrile neutropenia, differentiation syndrome, nausea, and hypokalemia. Adverse reactions leading to dose reduction occurred in 12% of patients who received REVUFORJ. Adverse reactions leading to a dose reduction (≥ 5%) included electrocardiogram QT prolonged. Adverse reactions leading to permanent discontinuation occurred in 20% of patients. Adverse reactions resulting in permanent discontinuation (> 1%) included infection.

The most common (≥ 20%) adverse reactions were phosphate increased, hemorrhage, nausea, infection without identified pathogen, aspartate aminotransferase increased, alanine aminotransferase increased, creatinine increased, musculoskeletal pain, febrile neutropenia, electrocardiogram QT prolonged, potassium decreased, parathyroid hormone intact increased, alkaline phosphatase increased, diarrhea, bacterial infection, triglycerides increased, differentiation syndrome, fatigue, edema, viral infection, phosphate decreased, decreased appetite, and constipation.

The common adverse reactions are summarised in Table 7.

Table 7. Adverse Reactions Reported in ≥ 20% (Any Grade) or ≥ 5% (Grade 3 or 4) in Patients with R/R Acute Leukemia
 | REVUFORJ N = 241
TEAE | All Grades % | Grade 3 or 4 %
Gastrointestinal disorders
Nauseaa | 48 | 5
Diarrheab | 29 | 5
Constipation | 20 | 0
Vascular disorders
Hemorrhage#,c | 48 | 10
Thrombosisd | 11 | 6
Infections and infestations
Infection without identified pathogene | 46 | 30
Bacterial infectionf | 27 | 18
Viral Infectiong | 23 | 6
Blood and lymphatic system disorders
Febrile neutropenia | 37 | 35
Musculoskeletal and connective tissue disorders
Musculoskeletal painh | 37 | 6
Investigations
Electrocardiogram QT prolonged | 36 | 17
Neoplasms benign, malignant and unspecified (including cysts and polyps)
Differentiation syndrome# | 25 | 12
General disorders and administration site conditions
Fatiguei | 24 | 5
Edemaj | 24 | 0
Metabolism and nutrition disorders
Decreased appetite | 20 | 5
# Includes the following fatal adverse reactions: DS (n=2); hemorrhage (n=2)
a – Includes nausea and vomiting
b – includes diarrhea, colitis, and neutropenic colitis
c – includes epistaxis, contusion, petechiae, gingival bleeding, hematoma, hemoptysis, hemorrhoidal hemorrhage, mouth hemorrhage, hematuria, ecchymosis, hemorrhage intracranial, subdural hematoma, upper gastrointestinal hemorrhage, gastrointestinal hemorrhage, vaginal hemorrhage, post- procedural hemorrhage, rectal hemorrhage, subarachnoid hemorrhage, vitreous hemorrhage, catheter site hemorrhage, conjunctival hemorrhage, hematochezia, melaena, retinal hemorrhage, anal hemorrhage, brain stem hemorrhage, cystitis hemorrhagic, eye hematoma, genital contusion, injection site hematoma, lower gastrointestinal hemorrhage, mucosal hemorrhage, oral blood blister, oral contusion, oral purpura, pulmonary hemorrhage, shock hemorrhagic, spinal subdural hematoma
d – includes disseminated intravascular coagulation, pulmonary embolism, cerebrovascular accident, superficial vein thrombosis, deep vein thrombosis, acute myocardial infarction, cerebral infarction, embolism, hemorrhoids thrombosed, medical device site thrombosis, myocardial infarction, renal infarction, splenic infarction, thrombosis, and transient ischaemic attack
e – includes pneumonia, sepsis, urinary tract infection, septic shock, sinusitis, skin infection, upper respiratory tract infection, osteomyelitis, device related infection, enterocolitis infectious, conjunctivitis, hordeolum, rhinitis, acute sinusitis, diverticulitis, endocarditis, perirectal abscess, rectal abscess, tooth abscess, abscess limb, appendicitis, bronchitis, epididymitis, eye infection, gastroenteritis, infection, mucosal infection, neutropenic sepsis, rash pustular, retinitis, shock, sialadenitis, soft tissue infection, tooth infection, vascular device infection
f – includes bacteraemia, clostridium difficile infection, cellulitis, escherichia bacteremia, paronychia, staphylococcal bacteremia, streptococcal bacteremia, alpha hemolytic streptococcal infection, clostridium difficile colitis, clostridium test positive, enterobacter infection, enterobacter sepsis, enterococcal bacteremia, escherichia urinary tract infection, pseudomonal bacteremia, pseudomonas infection, skin bacterial infection, bacteriuria, cellulitis staphylococcal, cornyebacterium bacteremia, enterobacter bacteremia, enterococcal infection, folliculitis, klebsiella infection, klebsiella sepsis, lactobacillus bacteremia, meningitis bacterial, stenotrophomonas infection
g – includes COVID-19, rhinovirus infection, herpes simplex reactivation, herpes simplex, herpes zoster, oral herpes, respiratory syncytial virus infection, enterovirus infection, adenovirus infection, coronavirus infection, cytomegalovirus infection, cytomegalovirus infection reactivation, cytomegalovirus viremia, COVID-19 pneumonia, cytomegalovirus test positive, enterovirus test positive, Epstein-Barr virus infection, herpes simplex pharyngitis, herpes virus infection, influenza, norovirus infection, parainfluenzae virus infection, pneumonia cytomegaloviral viremia
h – includes arthralgia, back pain, pain in extremity, neck pain, myalgia, musculoskeletal chest pain, myositis, flank pain, musculoskeletal discomfort, and musculoskeletal pain
i – includes fatigue, asthenia, malaise
j – includes edema peripheral, generalised edema, edema, localized edema, peripheral swelling

Clinically relevant adverse reactions in less than 20% of patients who received REVUFORJ include:

Cardiac disorders: Premature ventricular complex, cardiac failure, pericardial effusion, ventricular tachycardia, cardiac arrest

Endocrine disorders: Hyperparathyroidism

Eye disorders: Cataract

Gastrointestinal disorders: Abdominal pain

General disorders and administration site conditions: Sudden death

Immune system disorders: Drug hypersensitivity

Metabolism and nutrition disorders: Hyponatremia, hyperkalemia

Nervous system disorders: Taste disorder, syncope, headache, paresthesia

Renal disorders: Renal impairment

Skin and subcutaneous disorders: Rash

Changes in selected post-baseline laboratory values that were observed in patients with relapsed or refractory acute leukemia are shown in Table 8.

Table 8. Selected New or Worsening Laboratory Abnormalities in Patients with R/R Acute Leukemia
 | REVUFORJ
Laboratory Abnormality | Grades 1-4* % | Grades 3-4 %
Phosphate increased | 51 | -
Aspartate aminotransferase increased | 44 | 6
Alanine aminotransferase increased | 40 | 8
Creatinine increased | 38 | 2
Potassium decreased | 34 | 12
Parathyroid hormone, intact increased | 34 | -
Alkaline phosphatase increased | 33 | <1
Triglycerides increased | 27 | 3
Phosphate decreased | 25 | -
Cholesterol increased | 17 | 0
Calcium corrected increased | 15 | 0
*The denominator used to calculate the rate varied from 139 to 240 based on the number of patients with a baseline value and at least one post baseline value.

7 DRUG INTERACTIONS

7.1 Effect of Other Drugs on REVUFORJ

Strong CYP3A4 Inhibitors

If concomitant use of strong CYP3A4 inhibitors is required, reduce the REVUFORJ dosage [see Recommended Dosage (2.2)].

Revumenib is primarily metabolized by CYP3A4 [see Clinical Pharmacology (12.3)]. Concomitant use with a strong CYP3A4 inhibitor increases revumenib systemic exposure [see Clinical Pharmacology(12.3)], which may increase the risk of REVUFORJ adverse reactions.

Strong or Moderate CYP3A4 Inducers

Avoid concomitant use with strong or moderate CYP3A4 inducers.

Revumenib is primarily metabolized by CYP3A4 [see Clinical Pharmacology (12.3)]. Concomitant use with a strong or moderate CYP3A4 inducer may decrease revumenib and increase M1 systemic exposure [see Clinical Pharmacology (12.3)], which may reduce REVUFORJ efficacy or increase the risk of QT prolongation associated with the M1 metabolite.

Drugs that Prolong QTc Interval

Avoid concomitant use of REVUFORJ with other drugs with a known potential to prolong QTc interval. If concomitant use cannot be avoided, obtain ECGs when initiating, during concomitant use, and as clinically indicated [see Warnings and Precautions (5.2)]. Withhold REVUFORJ if the QTc interval is greater than 480 msec. Restart REVUFORJ after the QTc interval returns to less than or equal to 480 msec [see Dosage and Administration (2.3)].

REVUFORJ causes QTc interval prolongation [see Clinical Pharmacology (12.2)]. Concomitant use of REVUFORJ with other drugs that prolong QTc interval may result in an increase in the QTc interval and adverse reactions associated with QTc interval prolongation [see Warnings and Precautions(5.2)].

8 USE IN SPECIFIC POPULATIONS

8.1 Pregnancy

Risk Summary

Based on findings in animals and its mechanism of action[see Clinical Pharmacology (12.1)], REVUFORJ can cause fetal harm when administered to a pregnant woman. There are no available data on REVUFORJ use in pregnant women to evaluate for a drug-associated risk.

In an animal reproduction study, oral administration of revumenib to pregnant rats during the period of organogenesis caused adverse developmental outcomes, including embryo-fetal mortality, malformations, and altered fetal growth at maternal exposures approximately 0.5 times the human exposure (AUC) at the recommended dose (see Data). Advise pregnant women of the potential risk to a fetus.

In the U.S. general population, the estimated background risk of major birth defects and miscarriage in clinically recognized pregnancies is 2%-4% and 15%-20%, respectively.

Data

Animal Data

In an embryo-fetal development study, revumenib was administered once daily via oral gavage at doses of 30, 100, and 300 mg/kg/day to pregnant rats during the period of organogenesis (gestation days 6-17). Decreased maternal body weight gain and adverse embryo-fetal findings including decreases in the number of live fetuses, increases in resorptions and post-implantation loss, and decreases in fetal body weight were observed at all doses. At 300 mg/kg/day, total litter resorption and eye malformations were observed. At the dose of 30 mg/kg/day in rats, the maternal exposures (AUC) were approximately 0.5 times the human exposure at the recommended dose.

8.2 Lactation

Risk Summary

There are no data on the presence of revumenib or its metabolites in human milk or the effects on the breastfed child or milk production. Because of the potential for serious adverse reactions in a breastfed child, advise women not to breastfeed during treatment with REVUFORJ and for 1 week after the last dose.

8.3 Females and Males of Reproductive Potential

Based on findings in animals and its mechanism of action, REVUFORJ can cause fetal harm when administered to pregnant women [see Use in Specific Populations (8.1)].

Pregnancy Testing

Verify pregnancy status in females of reproductive potential within 7 days prior to initiating REVUFORJ.

Contraception

Females

Advise females of reproductive potential to use effective contraception during treatment with REVUFORJ and for 4 months after the last dose.

Males

Advise males of reproductive potential to use effective contraception during treatment with REVUFORJ and for 4 months after the last dose.

Infertility
Females and Males

Based on findings in animals, REVUFORJ may impair fertility. The effects on fertility were reversible [see Nonclinical Toxicology (13.1)].

8.4 Pediatric Use

The safety and efficacy of REVUFORJ have been established in pediatric patients 1 year and older with relapsed or refractory acute leukemia with a KMT2A translocation or an NPM1 mutation. Use of REVUFORJ for this indication is supported by evidence from adequate and well-controlled trials in adults and pediatric patients [see Clinical Studies (14)] and additional pharmacokinetic and safety data in pediatric patients [see Adverse Reactions (6.1) and Clinical Pharmacology (12.3)]. The patients included 25 infants (age < 2 years), 78 children (age 2 to < 12 years) and 29 adolescents (age 12 to < 17 years). The recommended dosage in patients weighing less than 40 kg is BSA-based.

The safety and efficacy of REVUFORJ in pediatric patients less than 1 year old have not been established.

Animal Data

In a repeat dose toxicity study in 6-7 week-old rats treated with revumenib at 75, 150, or 300 mg/kg/day for 13 weeks, an irreversible increase in femur growth plate closure was observed at revumenib exposures approximately 2 times the human exposure (AUC) at the recommended dose.

Based on the findings in animals, monitor bone growth and development in pediatric patients.

8.5 Geriatric Use

Of the 241 patients with relapsed or refractory acute leukemia with a KMT2A translocation or an NPM1 mutation in clinical studies of REVUFORJ, 61 (25%) patients were 65 years of age and older and 25 (10%) patients were 75 years of age and older [see Clinical Studies (14)].

No overall differences were observed in the effectiveness of REVUFORJ between patients who were 65 years and older and younger patients [see Clinical Studies (14.1) and Clinical Pharmacology (12.3)]. Compared to younger patients, the incidences of QTc prolongation and edema were higher in patients 65 years and older [see Warnings and Precautions (5.2)].

11 DESCRIPTION

REVUFORJ contains revumenib, a menin inhibitor. Revumenib is present as revumenib citrate hydrate with a chemical name of benzamide, N-ethyl-2-[[4-[7-[[trans-4- [(ethylsulfonyl)amino]cyclohexyl]methyl]-2,7-diazaspiro[3.5]non-2-yl]-5-pyrimidinyl]oxy]-5-fluoro-N-[1- methylethyl]-, 2-hydroxypropane-1,2,3-tricarboxylic acid, hydrate (1:1:1). The molecular formula is C32H47FN6O4S●C6H8O7●H2O with a molecular weight 840.96 g/mol.

Revumenib citrate hydrate is a white to faint pink solid. Revumenib citrate hydrate is soluble at pH 1.2 and 6.8, and sparingly soluble at pH 4.5.

The chemical structure is shown in Figure 1.

Figure 1: Chemical structure of Revumenib Citrate

REVUFORJ is available as tablets for oral use.

Each 25 mg strength tablet contains 25 mg revumenib, equivalent to 33.4 mg revumenib citrate, and the following inactive ingredients: microcrystalline cellulose, dicalcium phosphate, crospovidone, hypromellose, sodium bicarbonate, hydrophobic colloidal silica, magnesium stearate, polyvinyl alcohol, titanium dioxide, polyethylene glycol, talc, and red iron oxide.

Each 110 mg strength tablet contains 110 mg revumenib, equivalent to 146.5 mg revumenib citrate, and the following inactive ingredients: microcrystalline cellulose, dicalcium phosphate, crospovidone, hypromellose, sodium bicarbonate, hydrophobic colloidal silica, magnesium stearate, polyvinyl alcohol, titanium dioxide, polyethylene glycol, talc, red iron oxide, and yellow iron oxide.

Each 160 mg strength tablet contains 160 mg revumenib equivalent to 213.2 mg revumenib citrate, and the following inactive ingredients: microcrystalline cellulose, dicalcium phosphate, crospovidone, hypromellose, sodium bicarbonate, hydrophobic colloidal silica, magnesium stearate, polyvinyl alcohol, titanium dioxide, polyethylene glycol, talc, red iron oxide, and FD&C blue #2/indigo carmine aluminum lake.

12 CLINICAL PHARMACOLOGY

12.1 Mechanism of Action

Revumenib is a menin inhibitor that blocks the interaction of both wild-type lysine methyltransferase 2A (KMT2A) and KMT2A fusion proteins with menin. The binding of wild-type KMT2A or KMT2A fusion proteins with menin is involved in NPM1 mutated acute myeloid leukemias and KMT2A- rearranged acute leukemias, respectively, through activation of a leukemogenic transcriptional pathway. Susceptible NPM1 mutations are defined as those that result in loss of the nucleolar localization signal and the insertion of a new nuclear export signal leading to the accumulation of mutant NPM1 in the cytoplasm of AML cells. The most common of such NPM1 mutations in patients with AML are Types A, B, and D.

In nonclinical studies using cells that express KMT2A fusions, inhibition of the menin-KMT2A interaction with revumenib altered the transcription of multiple genes including differentiation markers. In nonclinical in vitro and in vivo studies, revumenib demonstrated antiproliferative and antitumor activity in leukemia cells harboring KMT2A fusion proteins. Revumenib also showed antiproliferative activity in vitro in leukemia cells with an NPM1 mutation.

12.2 Pharmacodynamics

Revumenib exposure-response relationships have not been fully characterized and the time course of pharmacodynamic response is unknown.

Cardiac Electrophysiology

The effect of REVUFORJ on the QTc interval was evaluated across a dose range of 113 mg to 339 mg twice daily (1.2 times the highest adult approved recommended dosage) with and without strong CYP3A4 inhibitors in patients with relapsed or refractory acute leukemia with a KMT2A translocation or an NPM1 mutation.

The increase in QTc interval was concentration dependent with an increase in QTc predicted to be 23 msec (upper bound of 90% confidence interval: 25 msec) at the mean steady-state maximum concentration (Cmax) observed in patients at the highest approved recommended dosage without strong CYP3A4 inhibitors. The increase in QTc interval was predicted to be 20 msec (upper bound of 90% confidence interval: 21 msec) at steady-state Cmax after administration of 160 mg twice daily with strong CYP3A4 inhibitors [see Warnings and Precautions (5.2)].

12.3 Pharmacokinetics

The pharmacokinetics of revumenib were characterized in patients with relapsed or refractory acute leukemia with a KMT2A translocation or an NPM1 mutation following single and multiple oral administration of revumenib with or without strong CYP3A4 inhibitors. Steady-state pharmacokinetic parameters are presented as geometric mean [coefficient of variation (%CV)] unless otherwise specified.

Table 9. Revumenib Pharmacokinetics in Patients with R/R Acute Leukemia with a KMT2A translocation or an NPM1 mutation
Parameter | Dosage
Parameter | 160 mg twice daily (with strong CYP3A4 inhibitors) | 270 mg twice daily (without strong CYP3A4 inhibitors)
General Information
Exposureba
Cmax (ng/mL) | 3028 (51%) | 2344 (81%)
AUC0-12h (ng•h/mL) | 20,050 (62%) | 11,520 (70%)
Dose Proportionalityb | Dose proportional increases in Cmax and AUC0-12h
Time to Steady-State | 2 days
Accumulationa | 2-fold
Absorption
Tmax Median (range) hours | 2 (0-12) | 1 (0.5-4)
Effect of Food
Low fat mealc | No clinically significant differences in revumenib pharmacokinetics observed (Cmax and AUC decreased by 27% and 12% respectively)
Distribution
Apparent Volume of Distributiona (L) | 63 (84%)
Protein Bindingd | 90%
Blood to plasma ratio | 0.8
Elimination
Half-Lifea (hours) | 6.4 (52%) | 3.0 (49%)
Apparent Clearancea (L/h) | 7 (64%) | 20 (112%)
Metabolism
Primary Pathway | CYP3A4
Active Metabolite | M1f
Excretionf
Feces | Approximately 52% (7% unchanged)
Urine | Approximately 25% (6% unchanged)
Abbreviations: Cmax = maximum plasma concentration; AUC = area under the time concentration curve;
Tmax = time to peak concentration
a - Steady-state
b - Dosage range of 113 mg to 339 mg (1.26 times the highest adult approved recommended dosage)
c - Approximately 400-500 calories, 25% of calories from fat
d - Independent of concentration
e - M1 contributes to revumenib’s clinically significant effects on QTc [see Warnings and Precautions (5.2) and Clinical Pharmacology (12.2)] but does not contribute to its efficacy at the approved recommended dosage
f - A single dose of radiolabeled revumenib 276 mg (1.02 times the highest adult approved recommended dosage) to adult patients with relapsed/refractory acute leukemia

Specific Populations

No clinically significant differences in the pharmacokinetics of revumenib were observed based on age (1 to 84 years), race (67% White, 7% Asian, 8% Black), sex, mild to moderate (CLcr 30 to 89 mL/min) renal impairment, and mild (total bilirubin ≤ upper limit of normal [ULN] and AST > ULN or total bilirubin > 1 to 1.5 × ULN and any AST) or moderate (total bilirubin > 1.5 to 3 × ULN and any AST) hepatic impairment. The effect of severe renal impairment (CLcr less than 30 mL/min), end- stage renal disease (CLcr less than 15 mL/min), or severe (total bilirubin > 3 × ULN and any AST) hepatic impairment is unknown.

Body weight (6-151 kg) has a significant effect on the pharmacokinetics of revumenib, with higher revumenib exposures in patients with lower body weight (less than 40 kg). This supports the use of BSA-based dosage in patients weighing less than 40 kg.

Pediatric Patients

Revumenib geometric mean (CV%) steady-state Cmax was 3137 (39%) ng/mL and AUC0-tau was 14,630 (55%) ng·hr/mL following 95 mg/m2 twice daily with strong CYP3A4 inhibitors.

Revumenib predicted geometric mean (%CV) steady-state Cmax was 1597 (70%) ng/mL and AUC0- tau was 12,570 (56%) ng·hr/mL following 160 mg/m2 twice daily without strong CYP3A4 inhibitors.

Drug Interaction Studies

Clinical Studies

Strong CYP3A4 Inhibitors:Revumenib AUC and Cmax is increased by 2-fold following concomitant use of multiple doses of revumenib with certain azole antifungals that are strong CYP3A4 inhibitors (i.e., posaconazole, itraconazole, and voriconazole). Similarly, revumenib AUC and Cmax is increased by 2.5-fold following concomitant use of multiple doses of revumenib with cobicistat (strong CYP3A4 inhibitor).

Strong and Moderate CYP3A4 Inducers:Revumenib exposure is expected to decrease and M1 exposure is expected to increase with strong and moderate CYP3A4 inducers.

Other Drugs:No clinically significant differences in revumenib pharmacokinetics were observed when used concomitantly with fluconazole (moderate CYP3A4 inhibitor), isavuconazole (moderate CYP3A4 inhibitor).

In Vitro Studies

Cytochrome P450 (CYP) Enzymes:Revumenib inhibits CYP3A4, but does not inhibit CYP1A2, CYP2A6, CYP2B6, CYP2C8, CYP2C9, CYP2C19, CYP2D6 and CYP2E1.

Revumenib does not induce CYP1A2, CYP2B6, and CYP3A4.

Transporter Systems:Revumenib is a substrate of OCT1, OCT2, OAT1, OAT3, and MATE1, but is not a substrate of P-gp, BCRP, OATP1B1, OATP1B3, MATE2-K, or BSEP. M1 is a substrate of OATP1B1, but is not a substrate of P-gp, BCRP, OCT2, OAT1, OAT3, OATP1B3, MATE1, or MATE2-K.

Revumenib inhibits MATE1, but does not inhibit P-gp, BCRP, OCT1, OCT2, OAT1, OAT3, OATP1B1, OATP1B3, BSEP, and MATE2-K. M1 inhibits MATE1, but does not inhibit OAT1, OAT3, OCT2, OATP1B1, OATP1B3, and MATE2-K.

13 NONCLINICAL TOXICOLOGY

13.1 Carcinogenesis, Mutagenesis, Impairment of Fertility

Carcinogenicity studies have not been conducted with revumenib. In a repeat dose toxicity study in rats treated with revumenib for 13 weeks, lymphoma was observed in multiple organs in one animal.

Revumenib was not genotoxic in an in vitro bacterial reverse mutation (Ames) assay, an in vitro micronucleus assay in human peripheral blood lymphocytes, or an in vivo rat peripheral blood reticulocyte micronucleus assay.

Fertility studies in animals have not been conducted with revumenib.

In a repeat dose toxicity study in dogs treated with revumenib at 12.5, 25 or 40 mg/kg/day for 13 weeks, microscopic findings in the testes and epididymis consisted of depletion of germ cells and decreased sperm at ≥12.5 mg/kg/day. In females, microscopic changes of atrophy in the mammary glands, uterus, and vagina and decreased number of corpora lutea in the ovaries were observed at ≥12.5 mg/kg/day. At the end of the 13-week recovery period, the findings in the female reproductive organs were reversed at all doses, and the testicular and epididymal effects were reversed at 12.5 mg/kg/day. At the dose of 12.5 mg/kg/day in dogs, exposures (AUC) were approximately 1.3 times the human exposure (AUC) at the recommended dose.

13.2 Animal Toxicology and/or Pharmacology

In a repeat dose toxicity study in dogs treated with revumenib at 12.5, 25, or 40 mg/kg/day for 13 weeks, microscopic findings of nerve fiber degeneration in the brain, sciatic nerves, and spinal cord segments were observed at ≥ 12.5 mg/kg/day and were not reversed at the end of a 13-week recovery period.

In a repeat dose toxicity study in rats treated with revumenib at 75, 150, 300 mg/kg/day for 13 weeks, dose dependent ocular findings of lens opacities were observed at ≥ 75 mg/kg/day; the findings progressed during the dosing and recovery periods and were not reversed.

Hyperplasia was observed in multiple organs including the testes, mammary gland, uterus, pancreas, and kidney in rats treated at ≥ 75 mg/kg/day for up to 13 weeks. The findings were irreversible in the testes, mammary gland, and pancreas. Revumenib exposures at 75 mg/kg/day in rats are approximately 2 times the human exposure (AUC) at the recommended dose.

14 CLINICAL STUDIES

14.1 Relapsed or Refractory Acute Leukemia with a KMT2A Translocation

SNDX-5613-0700

The efficacy of REVUFORJ was evaluated in a single-arm cohort of an open-label, multicenter trial (SNDX-5613-0700, NCT04065399; AUGMENT-101) in adult and pediatric patients at least 30 days old with relapsed or refractory (R/R) acute leukemia with a KMT2A translocation by local testing, including karyotyping. Patients with an 11q23 partial tandem duplication were excluded. Eligibility required a QTcF < 450 msec, estimated glomerular filtration rate ≥ 60 mL/min/1.73 m2, total bilirubin < 1.5 x the upper limit of normal (ULN), aminotransferases < 3 x ULN, and ejection fraction > 50% at study baseline. Eastern Cooperative Oncology Group performance status score was to be 0–2 if ≥ 18 years old, Karnofsky Performance Scale score ≥ 50 (if 16 to < 18 years old, and Lansky Performance score ≥ 50 if < 16 years old). Treatment consisted of REVUFORJ at a dose approximately equivalent to 160 mg in adults orally twice daily with a strong CYP3A4 inhibitor until disease progression, unacceptable toxicity, failure to achieve morphological leukemia-free state by 4 cycles of treatment, or hematopoietic stem cell transplantation (HSCT).

The baseline demographic and disease characteristics of the 104 treated patients are shown in Table 10. Twenty-four (23%) patients underwent HSCT following treatment with REVUFORJ.

Table 10. Baseline Demographic and Disease Characteristics in Patients with Relapsed or Refractory Acute Leukemia with KMT2A translocation (Study SNDX-5613-0700)
Demographic and Disease Characteristics | REVUFORJ; N = 104
Demographics
Median Age (years) (Range) | 37 (1, 79)
Age, n (%)
< 17 years old | 25 (24)
≥ 17 years old | 79 (76)
Sex, n (%)
Male | 37 (36)
Female | 67 (64)
Race, n (%)
Black or African American | 8 (8)
Asian | 10 (10)
White | 75 (72)
Multiple | 1 (1)
Unknown | 10 (10)
Ethnicity, n (%)
Hispanic or Latino | 23 (22)
Not Hispanic or Latino | 76 (73)
Unknown | 5 (5)
Disease Characteristics
Leukemia morphological type, n (%)
Acute myeloid leukemia (AML) | 86 (83)
Acute lymphoblastic leukemia (ALL) | 16 (15)
Mixed phenotype acute leukemia (MPAL) | 2 (2)
Translocations^1, n (%)
t(9;11) | 23 (22)
t(11;19) | 20 (19)
t(6;11) | 10 (10)
t(10;11) | 10 (10)
t(4;11) | 7 (7)
t(1;11) | 3 (3)
t(11;17) | 2 (2)
t(11;22) | 2 (2)
t(11;16) | 1 (1)
KMT2A fusion partner unknown | 26 (25)
Disease status, n (%)
Primary refractory | 22 (21)
Untreated relapse | 21 (20)
Refractory relapse | 61 (59)
Prior treatment
Number of prior regimens, median (range) | 2 (1, 11)
Prior stem cell transplantation, n (%) | 46 (44)
Number of prior relapses, n (%)
0 | 22 (21)
1 | 55 (53)
2 | 20 (19)
≥3 | 7 (7)
1. One patient did not have a translocation type reported.

Efficacy was established on the basis of the rate of complete remission (CR) plus CR with partial hematological recovery (CRh), the duration of CR+CRh, and the rate of conversion from transfusion dependence to transfusion independence. The median follow-up was 5.7 months (range, 0.3 to 28.9 months). The efficacy results are shown in Table 11. On subgroup analysis, CR+CRh was achieved by 18/86 (21%) of patients with AML, 3/16 (19%) of patients with ALL, and 1/2 (50%) of patients with MPAL.

Table 11. Efficacy Results in Patients with Relapsed or Refractory Acute Leukemia with KMT2A translocation (Study SNDX-5613-0700)
Endpoint | REVUFORJ N=104
CR^1+CRh^2 n (%) | 22 (21.2)
95% CI | (13.8, 30.3)^6
Median DOCR+CRh^3 (months) | 6.4^6
95% CI | (2.7, NE)
CR n (%) | 13 (12.5)
95% CI | (6.8, 20.4)^6
Median DOCR^4 (months) | 4.3^6
95% CI | (1.0, NE)
CRh n (%) | 9 (8.7)
95% CI | (4.0, 15.8)^6
Median DOCRh^5 (months) | 6.4^6
95% CI | (1.9, NE)
CI: confidence interval; NE = not estimable; DOCR = duration of CR; DOCRh = duration of CRh.
1. CR is defined as bone marrow blasts <5%; absence of circulating blasts and blasts with Auer rods; absence of extramedullary disease; ANC ≥1.0 × 109/L and platelet count ≥100 × 109/L.
2. CRh is defined as bone marrow blasts <5%; absence of circulating blasts and blasts with Auer rods; absence of extramedullary disease; residual neutropenia (>0.5 × 109/L) and thrombocytopenia (>50 × 109/L), but the count recovery criteria for CR are not met.
3. Duration of CR+CRh is defined as the time from first CR or CRh to the first documented relapse or death, whichever occurs first.
4. Duration of CR is defined as the time from first CR to the first documented relapse or death, whichever occurs first.
5. Duration of CRh is defined as the time from first CRh to the first documented relapse or death, whichever occurs first.
6. The 95% CI of the response rate is derived using the exact method based on binomial distribution. The median of the response duration is derived using Kaplan-Meier method.

For the 22 patients who achieved a CR or CRh, the median time to CR or CRh was 1.9 months (range: 0.9, 5.6 months).

Of the 83 patients who were dependent on red blood cell (RBC) and/or platelet transfusions at baseline, 12 (14%) became independent of RBC and platelet transfusions during any 56-day post- baseline period. Of the 21 patients who were independent of both RBC and platelet transfusions at baseline, 10 (48%) remained transfusion independent during any 56-day post-baseline period.

14.2 Relapsed or Refractory Acute Myeloid Leukemia with an NPM1 Mutation

SNDX-5613-0700

The efficacy of REVUFORJ was evaluated in a single-arm cohort of an open-label, multicenter trial (SNDX-5613-0700, NCT04065399; AUGMENT-101) described above [see Clinical Studies (14.1)]. A susceptible mutation was confirmed in enrolled patients using next generation sequencing or polymerase chain reaction (PCR) of the last exon of NPM1. The baseline demographic and disease characteristics of the 65 patients in the pivotal cohort are shown in Table 12. Seven patients (11%) underwent HSCT following treatment with REVUFORJ.

Table 12. Baseline Demographic and Disease Characteristics in Patients with Relapsed or Refractory Acute Myeloid Leukemia with an NPM1 Mutation (Study SNDX-5613-0700)
Demographic and Disease Characteristics | N = 65
Demographics
Median Age (years) (Range) | 65 (11, 84)
Age, n (%)
< 17 years old | 1 (1.5)
17 to < 65 years old | 31 (47.7)
65 years old | 33 (50.8)
Sex, n (%)
Male | 26 (40.0)
Female | 39 (60.0)
Race, n (%)
Black or African American | 6 (9.2)
Asian | 4 (6.2)
White | 38 (58.5)
Multiple | 1 (1.5)
Other | 3 (4.6)
Unknown | 13 (20.0)
Ethnicity
Hispanic or Latino | 5 (7.7)
Not Hispanic or Latino | 50 (76.9)
Not Reported | 9 (13.8)
Missing | 1 (1.5)
Disease Characteristics
NPM1 mutation type
Type A | 43 (66.2)
Type B | 4 (6.2)
Type D | 4 (6.2)
Non-A, B, or D | 5 (7.7)
Not Available | 9 (13.8)
Prior treatment
Median number of prior regimens (min, max) | 2 (1, 7)
Prior stem cell transplantation, n (%) | 15 (23.1)

Efficacy was established on the basis of the rate of complete remission (CR) plus CR with partial hematological recovery (CRh), the duration of CR+CRh, and the rate of conversion from transfusion dependence to transfusion independence. The median follow-up was 3.8 months (range, 0.1 to 29.9) months. The efficacy results are shown in Table 13.

Table 13. Efficacy Results in Patients with Relapsed or Refractory Acute Myeloid Leukemia with an NPM1 mutation (Study SNDX-5613-0700)
Endpoint | REVUFORJ N = 65
CR^1+CRh^2 n (%) | 15 (23.1)
95% CI | (13.5, 35.2)^6
Median DOCR+CRh^3 (months) | 4.5^6
95% CI | (1.2, 8.1)
CR n (%) | 12 (18.5)
95% CI | (9.9, 30)^6
Median DOCR^4 (months) | 3.7^6
95% CI | (1.0, 8.1)
CRh n (%) | 3 (4.6)
95% CI | (1.0, 12.9)^6
Observed DOCRh^5 (months) | 1.8, 2.0, 4.5
CI: confidence interval; NE = not estimable; DOCR = duration of CR; DOCRh = duration of CRh.
1. CR is defined as bone marrow blasts <5%; absence of circulating blasts and blasts with Auer rods; absence of extramedullary
disease; ANC ≥1.0 × 109/L and platelet count ≥100 × 109/L.
2. CRh is defined as bone marrow blasts <5%; absence of circulating blasts and blasts with Auer rods; absence of extramedullary
disease; residual neutropenia (>0.5 × 109/L) and thrombocytopenia (>50 × 109/L), but the count recovery criteria for CR are not met.
3. Duration of CR+CRh is defined as the time from first CR or CRh to the first documented relapse or death, whichever occurs first.
4. Duration of CR is defined as the time from first CR to the first documented relapse or death, whichever occurs first.
5. Duration of CRh is defined as the time from first CRh to the first documented relapse or death, whichever occurs first.
6. The 95% CI of the response rate is derived using the exact method based on binomial distribution. The median of the response duration is derived using Kaplan-Meier method.

For the 15 patients who achieved a CR or CRh, the median time to response was 2.8 months (range: 1.8, 9.6 months).

Of the 46 patients who were dependent on red blood cell (RBC) and/or platelet transfusions at baseline, 8 (17%) became independent of RBC and platelet transfusions during any 56-day post- baseline period. Of the 19 patients who were independent of both RBC and platelet transfusions at baseline, 13 (68%) remained transfusion independent during any 56-day post-baseline period.

16 HOW SUPPLIED/STORAGE AND HANDLING

25 mg: Pink modified oval film-coated tablet debossed with “S” on one side and “25” on the other side.

- 30-count bottles with a desiccant and child resistant closure (NDC 73555-500-00)

110 mg: Beige modified oval film-coated tablet debossed with “S” on one side and “110” on the other side.

- 30-count bottles with a desiccant and child resistant closure (NDC 73555-501-00)

160 mg: Purple modified oval film-coated tablet debossed with “S” on one side and “160” on the other side.

- 30-count bottles with a desiccant and child resistant closure (NDC 73555-502-00)

STORAGE AND HANDLING

Store tablets at 20°C to 25°C (68°F to 77°F); excursions permitted between 15°C to 30°C (59°F to 86°F) [see USP Controlled Room Temperature].

Store and dispense in the orginal container.

17 PATIENT COUNSELING INFORMATION

Advise the patient to read the FDA-approved patient labeling (Medication Guide) and Instructions for Use.

Differentiation Syndrome

Advise patients of the risks of developing differentiation syndrome as early as 3 days after the start of therapy and during treatment. Ask patients to immediately report any symptoms suggestive of differentiation syndrome, such as fever, cough or difficulty breathing, rash, low blood pressure, rapid weight gain, swelling of their arms or legs, or decreased urinary output, to their healthcare provider for further evaluation [see Boxed Warning and Warnings and Precautions (5.1)].

Prolonged QT Interval and Torsades de Pointes

Advise patients to consult their healthcare provider immediately if they feel faint, lose consciousness, or have signs or symptoms suggestive of arrhythmia. Advise patients with a history of hypokalemia or hypomagnesemia of the importance of monitoring their electrolytes [see Boxed Warning and Warnings and Precautions (5.2)].

Embryo-Fetal Toxicity

Advise pregnant women and females of reproductive potential of the potential risk to a fetus. Advise females of reproductive potential to notify their healthcare provider of a known or suspected pregnancy [see Warnings and Precautions (5.3) and Use in Specific Populations (8.1)].

Advise females of reproductive potential to use effective contraception during treatment with REVUFORJ and for 4 months after the last dose. Advise males with female partners of reproductive potential to use effective contraception during treatment with REVUFORJ and for 4 months after the last dose [see Use in Specific Populations (8.3)].

Lactation

Advise women not to breastfeed during treatment with REVUFORJ and for 1 week after the last dose [see Use in Specific Populations (8.2)].

Infertility

Advise females and males of reproductive potential of the potential for impaired fertility from REVUFORJ [see Use in Specific Populations (8.3), Nonclinical Toxicology (13.1)].

Drug Interactions

Advise patients to inform their healthcare providers of all concomitant products, including over-the counter products and supplements [see Drug Interactions (7.1)].

Dosing Instructions

Advise patients to swallow tablets whole with a cup of water and not to cut or chew tablets. If patients are unable to swallow the tablets, they may be crushed and dispersed in water [see Instructions for Use]. Instruct patients that, if they miss a dose of REVUFORJ, to take it as soon as possible on the same day, and at least 12 hours prior to the next scheduled dose, and return to the normal schedule the following day [see Dosage and Administration (2.2)].

Manufactured for
Syndax Pharmaceuticals, Inc., New York, NY 10017

REVUFORJ ® is a registered trademark of Syndax Pharmaceuticals, Inc.

© 2025 Syndax Pharmaceuticals, Inc.

218944-SYND-USPI-003

Medication Guide

REVUFORJ (REV-you-forge)

(revumenib)

tablets, for oral use

What is the most important information I should know about REVUFORJ?
REVUFORJ may cause serious side effects including:

- differentiation syndrome. Differentiation syndrome is a serious, but common condition that affects your blood cells which may be life threatening or lead to death if not treated. Differentiation syndrome has happened as early as 3 days and up to 41 days after starting REVUFORJ. Tell any healthcare provider caring for you that you are taking a medicine that can cause differentiation syndrome. Call your healthcare provider or go to the nearest hospital emergency room right away if you develop any of the following symptoms of differentiation syndrome during treatment with REVUFORJ:

- fever
- cough
- shortness of breath
- severe headache
- confusion

- dizziness or lightheadedness
- fast weight gain
- swelling of arms, legs, neck, groin, or underarm area
- decreased urination
- rash

If you develop any of these symptoms of differentiation syndrome, your healthcare provider may start you on a medicine given through a vein (intravenous) called corticosteroids and may monitor you in the hospital.

- changes in electrical activity of your heart called QT prolongation. QT prolongation is a serious, but common side effect that can cause irregular heartbeats that can be life-threatening, such as a heart attack, and can lead to death. Your healthcare provider will check the electrical activity of your heart with a test called an electrocardiogram (ECG) and will also do blood tests to check your potassium and magnesium levels before and during treatment with REVUFORJ. Tell your healthcare provider right away if you feel faint, lightheaded, dizzy, or if you feel your heart beating irregularly or fast during treatment with REVUFORJ.

See "What are the possible side effects of REVUFORJ?" for more information about side effects.

What is REVUFORJ?

REVUFORJ is a prescription medicine used to treat adults and children 1 year and older with:

- acute leukemia with a lysine methyltransferase 2A gene (KMT2A) translocation whose disease has come back or has not improved after previous treatment(s).
- acute myeloid leukemia with a nucleophosmin 1 (NPM1) mutation whose disease has come back or has not improved after previous treatment(s) and who have no other satisfactory treatment options

Your healthcare provider will perform a test to make sure that REVUFORJ is right for you.
It is not known if REVUFORJ is safe and effective in children less than 1 year of age.

Before taking REVUFORJ, tell your healthcare provider about all of your medical conditions, including if you:

- have any heart problems, including a condition called long QT syndrome.
- have been told you have low blood levels of potassium or magnesium.
- are pregnant or plan to become pregnant. REVUFORJ can harm your unborn baby.

Females who are able to become pregnant:

o Your healthcare provider will perform a pregnancy test within 7 days before you start treatment with REVUFORJ.
o Tell your healthcare provider right away if you become pregnant or think you may be pregnant during treatment with REVUFORJ.
o Use effective birth control (contraception) during treatment with REVUFORJ and for 4 months after the last dose of REVUFORJ.

Males who have female partners who are able to become pregnant:

o Use effective birth control during treatment with REVUFORJ and for 4 months after the last dose of REVUFORJ.
o Talk to your healthcare provider about birth control methods you can use during this time.

- are breastfeeding or plan to breastfeed. It is not known if REVUFORJ passes into your breast milk. Do not breastfeed during your treatment with REVUFORJ or for 1 week after your last dose of REVUFORJ.

Tell your healthcare provider about any other medicines you take, including prescription and over-the-counter medicines, vitamins, and herbal supplements.

REVUFORJ and other medicines may affect each other causing side effects.

Know the medicines you take. Keep a list of them to show your healthcare provider and pharmacist when you get a new medicine.

How should I take REVUFORJ?

- Take REVUFORJ exactly as your healthcare provider tells you to. Do not change your dose or stop taking REVUFORJ unless your healthcare provider tells you to.
- REVUFORJ tablets come in different strengths. Each strength is a different color. Your healthcare provider may prescribe more than 1 strength of REVUFORJ tablets for you, so it is important that you understand how to take your medicine the right way. Be sure that you understand exactly how many tablets you need to take, and what strengths to take.
- Take REVUFORJ 2 times a day at about the same time each day about 12 hours apart.
- Take REVUFORJ fasted (on an empty stomach) or with a low-fat meal (400 calories, 25% or less fat). Talk to your healthcare provider about examples of low-fat meals that you can eat.
- Swallow REVUFORJ tablets whole with a cup of water. Do not cut or chew tablets. If you are unable to swallow tablets, crush the tablets and break them apart in water. See the Instructions for Use for detailed instructions on how to prepare and give REVUFORJ tablets.
- If you miss a dose of REVUFORJ or did not take it at the usual time, take your dose as soon as possible and at least 12 hours before your next dose. Do not take 2 doses within 12 hours. Return to your normal scheduled dose the following day.

What are the possible side effects of REVUFORJ?

REVUFORJ may cause serious side effects including:

- see “What is the most important information I should know about REVUFORJ?”

The most common side effects of REVUFORJ include:

- infections, including bacterial and viral infections
- changes in liver function tests
- bleeding (hemorrhage)
- nausea and vomiting
- muscle pain
- low white blood cell counts with fever

- diarrhea
- tiredness
- swelling in the arms and legs
- decreased appetite
- constipation

Your healthcare provider may change your dose, temporarily stop, or permanently stop treatment with REVUFORJ if you develop certain side effects.

REVUFORJ may cause fertility problems in females and males, which may affect your ability to have children. Talk to your healthcare provider if this is a concern for you.

These are not all possible side effects of REVUFORJ.

Call your doctor for medical advice about side effects. You may report side effects to FDA at 1-800-FDA-1088.

How should I store REVUFORJ?

- Store REVUFORJ at room temperature between 68°F to 77°F (20°C to 25°C).
- Store the tablets in the bottle that it comes in until you are ready to take it.
- The REVUFORJ bottle has a drying agent (desiccant) and child resistant closure.

Keep REVUFORJ and all medicines out of reach of children.

General information about the safe and effective use of REVUFORJ.

Medicines are sometimes prescribed for purposes other than those listed in a Medication Guide. Do not use REVUFORJ for a condition for which it is not prescribed. Do not give REVUFORJ to other people, even if they have the same symptoms you have. It may harm them. You can ask your pharmacist or health professionals for information about REVUFORJ that is written for healthcare professionals.

What are the ingredients in REVUFORJ?

Active ingredient: revumenib

Inactive ingredients: microcrystalline cellulose, dicalcium phosphate, crospovidone, hypromellose, sodium bicarbonate, hydrophobic colloidal silica, magnesium stearate, polyvinyl alcohol, titanium dioxide, polyethylene glycol, talc, and red iron oxide.

The 110 mg tablet also includes yellow iron oxide.

The 160 mg tablet also includes FD&C blue #2/indigo carmine aluminum lake.

Manufactured for: Syndax Pharmaceuticals, Inc., New York, NY 10017

REVUFORJ ® is a registered trademark of Syndax Pharmaceuticals, Inc.

Copyright © 2025 Syndax Pharmaceuticals, Inc.

For more information, go to www.revuforj.com or call Syndax at 1-888-539-3REV.

218944-SYND-MG-003

This Medication Guide has been approved by the U.S. Food and Drug Administration.

Revised: 10/2025

INSTRUCTIONS FOR USE

REVUFORJ (REV-you-forge)

revumenib tablets, for oral use

Read these Instructions for Use to prepare and take or give a dose of REVUFORJ tablets broken apart (dispersed) in water and each time you or your child get a prescription refill. There may be new information. This information does not take the place of talking with your healthcare provider about you or your child’s medical condition or your treatment.

Important information you need to know before preparing to break apart the REVUFORJ tablets in water:

- For more information about REVUFORJ tablets, see the Medication Guide.
- REVUFORJ tablets broken apart in water should be prepared for people who are unable to swallow whole REVUFORJ tablets. People who can swallow the tablets whole should not cut, chew, or break the tablets apart in water.
- Take or give REVUFORJ tablets exactly as your healthcare provider tells you to. Do not change your dose or stop taking REVUFORJ unless your provider tells you to.
- REVUFORJ tablets come in different strengths. Each strength is a different color. Your healthcare provider may prescribe more than 1 strength of REVUFORJ tablets for you or your child, so it is important that you understand how to take or give the medicine the right way. Be sure that you understand exactly how many tablets you need to take, and what strengths to take.
- Check the expiration date on the REVUFORJ tablet bottles. Do not use REVUFORJ if the expiration date on the bottles have passed. Contact your healthcare provider or pharmacist.
- The REVUFORJ tablets should be crushed in a clean and dry pill crusher.
- Use room temperature water to dissolve the REVUFORJ tablets.
- Use a teaspoon to measure the room temperature water. Use a 20 mL oral syringe to administer the medicine.
  o Oral syringes can look different. Talk to your pharmacist if you are not sure if you have the correct oral syringe size.
  o Replace the oral syringe if there are signs of damage. See Step 15.

Supplies needed to prepare and break apart the REVUFORJ tablets in water. You will need to get the 20 mL oral syringe and pill crusher, which are available from your pharmacy.

Figure A

Preparing to dissolve the REVUFORJ tablets

Step 1: Gather and place the REVUFORJ bottles and supplies on a clean, flat surface.

Check your prescribed dose. Count out the strengths and number of REVUFORJ tablets needed for the prescribed dose.

Add all the REVUFORJ tablets to a clean and dry pill crusher. Screw the top of the pill crusher down until it touches the REVUFORJ tablets.

Turn the pill crusher cap back and forth to crush the REVUFORJ tablets. Continue turning the pill crusher cap back and forth, increasing the crushing pressure on the REVUFORJ tablets each time.

Repeat until all large REVUFORJ tablet pieces are broken up. The crushed REVUFORJ tablets should be like the consistency of flour.

Figure B

Step 2: Use two teaspoons to measure 10 mL of room temperature water. Add the 10 mL of water to the small cup.

Add water to the cup first and then add the crushed REVUFORJ tablets.

Do not add the crushed REVUFORJ tablets first followed by the room temperature water.

Figure C

Step 3: Tip the crushed REVUFORJ tablets from the pill crusher into the small cup that contains 10 mL of water. Carefully add all of the crushed REVUFORJ tablets to the small cup.

Hold the pill crusher upside down over the small cup. Tap the pill crusher to make sure no more crushed REVUFORJ tablet pieces are left in the pill crusher.

Figure D

Step 4: Carefully swirl the cup right after adding the crushed REVUFORJ tablets to the small cup with water. Swirl the small cup every 30 seconds to 1 minute for a total of 5 minutes.

The crushed REVUFORJ tablets in water will look cloudy.

Figure E

Step 5: Draw up the medicine into the 20 mL oral syringe right away.

Push the plunger of the oral syringe all the way up towards the tip. Place the tip of the oral syringe in the small cup. Pull the oral syringe plunger to draw up all of the medicine in the small cup.

The medicine must be taken within 2 hours of preparation. Turn the oral syringe upside down and back several times before taking or giving the medicine.

Figure F

Step 6: The adult or child should sit up straight or stand before taking the medicine.

Place the tip of the oral syringe into the mouth against the inside of the cheek. Slowly and gently press down on the plunger to gently squirt the medicine into the mouth. Allow the adult or child to swallow the medicine. Make sure that no medicine is left in the mouth.

The adult or child should remain sitting up straight or standing for 2 to 3 minutes right after receiving a dose of the medicine.

If the medicine is vomited or all of the medicine is not swallowed, do not give another dose. Wait until the next scheduled dose.

Figure G

Step 7: The small cup must be rinsed to make sure the adult or child receives the full dose of REVUFORJ tablets.

Place two teaspoons (10 mL) of room temperature water in the cup rinsing down the sides (Figure H)

Swirl the water around the sides of the small cup to make sure any remaining crushed REVUFORJ tablets is mixed with the water (Figure I).

Figure H

Figure I

Step 8: Repeat Step 5 and Step 6 until no more medicine is left in the cup.

Cleaning the oral syringe after use

Follow the instructions below for cleaning and storing the oral syringe (Step 9 through Step 15). Throw away the oral syringe in your household trash if it is damaged (See Step 15), and use a new 20 mL oral syringe.

Step 9: Remove the plunger from the barrel of the oral syringe.

Figure J

Step 10: Rinse the barrel and plunger in warm running water to help make sure all of the medicine has been removed from the oral syringe.

Do not boil the oral syringe.

Figure K

Step 11: Put the plunger into the barrel of the oral syringe.

Figure L

Step 12: Hold the oral syringe tip under water and draw warm water several times into the oral syringe and squirt out again until all of the medicine has been removed from the oral syringe. Repeat this Step until the oral syringe is clean.

Figure M

Step 13: Remove the plunger from the barrel of the oral syringe. Rinse the barrel and plunger again with warm water.

Figure N

Step 14: Shake off excess water or wipe off the outside of the plunger and barrel. Place the barrel and plunger on a clean, dry paper towel to dry.

Figure O

Step 15: Make sure the oral syringe parts are fully dry before putting the plunger back into the barrel of the oral syringe. Store the oral syringe in a clean place until the next use.

Replace the oral syringe if:

- there is any damage to the barrel, plunger, or tip.
- you cannot see the dosage markings or it becomes difficult to move the plunger.

Cleaning the pill crusher after use

Step 16: Rinse both parts of the pill crusher with water after use. Shake off excess water or wipe both parts of the pill crusher. Place both parts of the pill crusher on a clean, dry paper towel to dry.

Storing REVUFORJ

- Store REVUFORJ at room temperature between 68°F to 77°F (20°C to 25°C).
- Store the tablets in the bottle that it comes in until you are ready to take it.
- The REVUFORJ bottle has a drying agent (desiccant) and child resistant closure.

Keep REVUFORJ and all medicines out of reach of children.

Manufactured for: Syndax Pharmaceuticals, Inc., New York, NY 10017
REVUFORJ ® is a registered trademark of Syndax Pharmaceuticals, Inc.
Copyright © 2025 Syndax Pharmaceuticals, Inc.
For more information, go to www.revuforj.com or call Syndax at 1-888-539-3REV.
218944-SYND-IFU-003

This Instructions for Use has been approved by the U.S. Food and Drug Administration.

Revised: 10/2025

Revuforj 25 mg carton/container labels

Principle Display Panel

30 tablets

Revuforj®
(revumenib) tablets

25 mg

Dispense enclosed Medication Guide to each patient.

Swallow tablets whole or crush and disperse in water.
Do not cut or chew tablets.

Syndax Rx Only

This bottle contains 30 tablets (25 mg each) of Revuforj®

revumenib. Swallow tablets whole or crush and (revumenib) tablets Keep out of
disperse in water. Do not cut or chew tablets. 25 mg the reach of
Store at 20°C to 25°C (68°F to 77°F); excursions children.
permitted between 15°C to 30°C (59°F to 86°F).
Recommended dosage: See Prescribing information.
Manufactured for: Syndax Pharmaceuticals, Inc. Syndax Rx Only 30 tablets

Revuforj 110 mg carton/container labels

Principle Display Panel

30 tablets

Revuforj®
(revumenib) tablets

110 mg

Dispense enclosed Medication Guide
to each patient.

Swallow tablets whole or crush and
disperse in water. Do not cut or
chew tablets.

Syndax Rx Only

This bottle contains 30 tablets

(110 mg each) of revumenib. 30 tablets

Swallow tablets whole or crush
and disperse in water. Do not cut or
chew tablets. Revuforj®

Store at 20°C to 25°C (68°F to 77°F); (revumenib) tablets
excursions permitted between 15°C
to 30°C (59°F to 86°F). 110 mg

Recommended dosage:
See Prescribing information.

Keep out of the reach of children.

Manufactured for: Syndax Rx Only
Syndax Pharmaceuticals, Inc.

Revuforj 160 mg carton/container labels

Principle Display Panel

30 tablets

Revuforj®
(revumenib) tablets

160 mg

Dispense enclosed Medication Guide
to each patient.

Swallow tablets whole or crush and
disperse in water. Do not cut or
chew tablets.

Syndax Rx Only

This bottle contains 30 tablets

(160 mg each) of revumenib. 30 tablets

Swallow tablets whole or crush
and disperse in water. Do not cut or
chew tablets. Revuforj®

Store at 20°C to 25°C (68°F to 77°F); (revumenib) tablets
excursions permitted between 15°C
to 30°C (59°F to 86°F). 160 mg

Recommended dosage:
See Prescribing information.

Keep out of the reach of children.

Manufactured for: Syndax Rx Only
Syndax Pharmaceuticals, Inc.